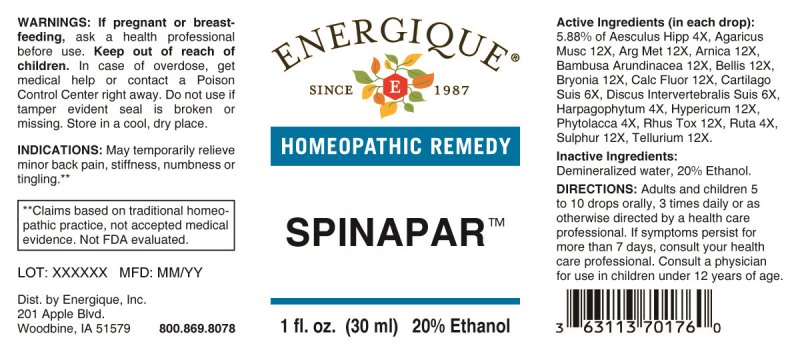 DRUG LABEL: Spinapar
NDC: 44911-0659 | Form: LIQUID
Manufacturer: Energique, Inc.
Category: homeopathic | Type: HUMAN OTC DRUG LABEL
Date: 20241030

ACTIVE INGREDIENTS: HORSE CHESTNUT 4 [hp_X]/1 mL; HARPAGOPHYTUM PROCUMBENS ROOT 4 [hp_X]/1 mL; PHYTOLACCA AMERICANA ROOT 4 [hp_X]/1 mL; RUTA GRAVEOLENS FLOWERING TOP 4 [hp_X]/1 mL; SUS SCROFA CARTILAGE 6 [hp_X]/1 mL; SUS SCROFA INTERVERTEBRAL DISC 6 [hp_X]/1 mL; AMANITA MUSCARIA FRUITING BODY 12 [hp_X]/1 mL; SILVER 12 [hp_X]/1 mL; ARNICA MONTANA WHOLE 12 [hp_X]/1 mL; BAMBUSA BAMBOS LEAF 12 [hp_X]/1 mL; BAMBUSA BAMBOS SAP 12 [hp_X]/1 mL; BELLIS PERENNIS WHOLE 12 [hp_X]/1 mL; BRYONIA ALBA ROOT 12 [hp_X]/1 mL; CALCIUM FLUORIDE 12 [hp_X]/1 mL; HYPERICUM PERFORATUM WHOLE 12 [hp_X]/1 mL; TOXICODENDRON PUBESCENS LEAF 12 [hp_X]/1 mL; SULFUR 12 [hp_X]/1 mL; TELLURIUM 12 [hp_X]/1 mL
INACTIVE INGREDIENTS: WATER; ALCOHOL

DRUG FACTS:

ACTIVE INGREDIENTS:

(in each drop): 5.88% of Aesculus Hippocastanum 4X, Agaricus Muscarius 12X, Argentum Metallicum 12X, Arnica Montana 12X, Bambusa Arundinacea 12X, Bellis Perennis 12X, Bryonia (Alba) 12X, Calcarea Fluorica 12X, Cartilago Suis 6X, Discus Intervertebralis Suis 6X, Harpagophytum 4X, Hypericum Perforatum 12X, Phytolacca Decandra 4X, Rhus Tox 12X, Ruta Graveolens 4X, Sulphur 12X, Tellurium Metallicum 12X.

INDICATIONS:

May temporarily relieve minor back pain, stiffness, numbness or tingling.**

**Claims based on traditional homeopathic practice, not accepted medical evidence. Not FDA evaluated.

WARNINGS:

If pregnant or breast-feeding, ask a health professional before use.

Keep out of reach of children. In case of overdose, get medical help or contact a Poison Control Center right away.

Do not use if tamper evident seal is broken or missing. Store in a cool, dry place.

Keep out of reach of children. In case of overdose, get medical help or contact a Poison Control Center right away.

DIRECTIONS:

Adults and children 5 to 10 drops orally, 3 times daily or as otherwise directed by a health care professional. If symptoms persist for more than 7 days, consult your health care professional. Consult a physician for use in children under 12 years of age.

INDICATIONS:

May temporarily relieve minor back pain, stiffness, numbness or tingling.**

**Claims based on traditional homeopathic practice, not accepted medical evidence. Not FDA evaluated.

INACTIVE INGREDIENTS:

Demineralized water, 20% Ethanol.

QUESTIONS:

Dist. by Energique, Inc.

201 Apple Blvd.

Woodbine, IA 51579 800-869-8078

PACKAGE LABEL DISPLAY:

ENERGIQUE

SINCE 1987

HOMEOPATHIC REMEDY

SPINAPAR

1 fl. oz. (30 ml)